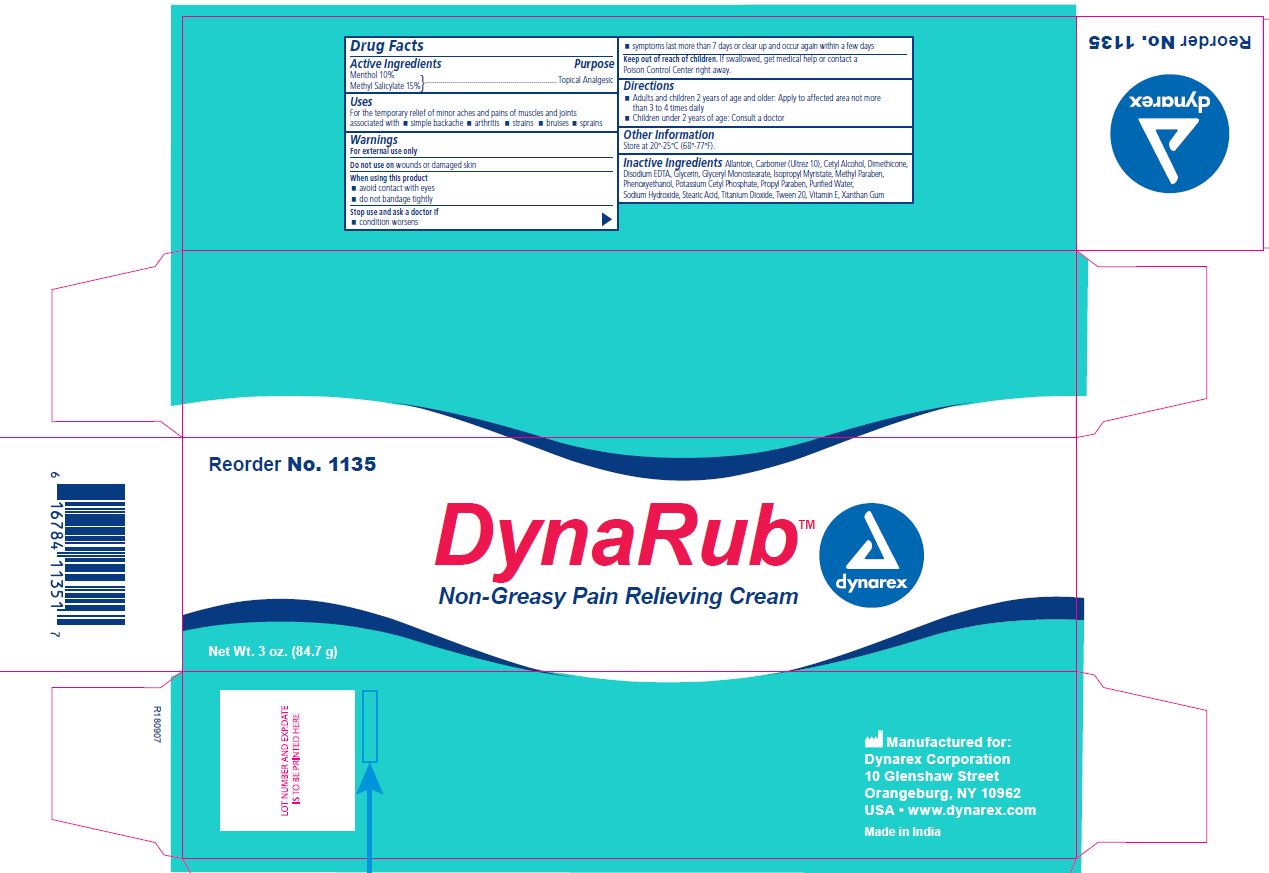 DRUG LABEL: DynaRub
NDC: 67777-113 | Form: CREAM
Manufacturer: Dynarex Corporation
Category: otc | Type: HUMAN OTC DRUG LABEL
Date: 20241120

ACTIVE INGREDIENTS: MENTHOL 10 g/100 g; METHYL SALICYLATE 15 g/100 g
INACTIVE INGREDIENTS: GLYCERIN; GLYCERYL MONOSTEARATE; ISOPROPYL MYRISTATE; METHYLPARABEN; PHENOXYETHANOL; SODIUM HYDROXIDE; STEARIC ACID; EDETATE DISODIUM ANHYDROUS; WATER; ALLANTOIN; CARBOXYPOLYMETHYLENE; DIMETHICONE; CETYL ALCOHOL; TITANIUM DIOXIDE; ALPHA-TOCOPHEROL ACETATE; XANTHAN GUM; POTASSIUM CETYL PHOSPHATE; PROPYLPARABEN; POLYSORBATE 20

1135 - DynaRub NDC 67777-113-50

Active Ingredient

Menthol 10%

Purpose

Topical Analgesic

Active Ingredient

Methyl Salicylate 15%

Purpose

Topical Analgesic

Uses

For the temporary relief of minor aches and pains of muscles and joints associated with simple backache, arthritis, strains, bruises, sprains

Warnings

For external use only

Do not use on

wounds or damaged skin

When using this product

- avoid contact with eyes
- do not bandage tightly

Stop use and ask a doctor if

- condition worsens
- symptoms last more than 7 days or clear up and occur again within a few days

KEEP OUT OF REACH OF CHILDREN

If swallowed, get medical help or contact a Poison Control Center right away.

Directions

- Adults and children 2 years of age and older: Apply to affected area not more than 3 to 4 times daily
- Children under 2 years of age: Consult a doctor

Other Information

store at 20°-25°C (68°-77°F).

Inactive Ingredients

Allantoin, Carbomer (Ultrez 10), Cetyl Alcohol, Dimethicone, Disodium EDTA, Glycerin, Glyceryl Monostearate, Isopropyl Myristate, Methyl Paraben, Phenoxyethanol, Potassium Cetyl Phosphate, Propyl Paraben, Purified Water, Sodium Hydroxide, Stearic Acid, Titanium Dioxide, Tween 20, Vitamin E, Xanthan Gum